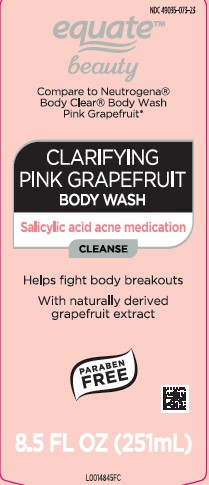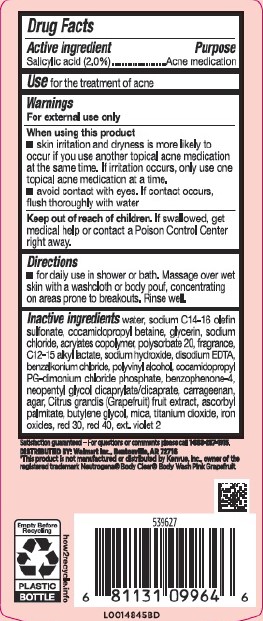 DRUG LABEL: Body Wash
NDC: 49035-073 | Form: GEL
Manufacturer: Walmart Inc.
Category: otc | Type: HUMAN OTC DRUG LABEL
Date: 20260227

ACTIVE INGREDIENTS: SALICYLIC ACID 20 mg/1 mL
INACTIVE INGREDIENTS: WATER; SODIUM C14-16 OLEFIN SULFONATE; COCAMIDOPROPYL BETAINE; GLYCERIN; SODIUM CHLORIDE; BUTYL ACRYLATE/METHYL METHACRYLATE/METHACRYLIC ACID COPOLYMER (18000 MW); POLYSORBATE 20; C12-15 ALKYL LACTATE; SODIUM HYDROXIDE; EDETATE DISODIUM; BENZALKONIUM CHLORIDE; POLYVINYL ALCOHOL, UNSPECIFIED; COCAMIDOPROPYL PROPYLENE GLYCOL-DIMONIUM CHLORIDE PHOSPHATE; SULISOBENZONE; NEOPENTYL GLYCOL DICAPRYLATE/DICAPRATE; CARRAGEENAN; AGAR, UNSPECIFIED; PUMMELO; ASCORBYL PALMITATE; BUTYLENE GLYCOL; MICA; TITANIUM DIOXIDE; FERRIC OXIDE RED; D&C RED NO. 30; FD&C RED NO. 40; EXT. D&C VIOLET NO. 2

Equate 353.001/353AE
Clarifying Body Wash Pink Grapefruit

Active ingredient

Salicylic acid (2.0%)

Purpose

Acne medication

Use

For the treatment of acne

Warnings

For external use only

When using this product

- skin irritation and dryness is more likely to occur if you use another topical acne medication at the same time. If irritation occurs, only use one topical acne medication at a time.
- avoid contact with the eyes. If contact occurs, flush thoroughly with water.

Keep out of reach of children.

If swallowed, get medical help or contact a Poison Control Center right away.

Directions

- for daily use in shower or bath. Massage over wet skin with a washcloth or body pouf, concentrating on areas prone to breakouts. Rinse well.

Inactive ingredients

water, sodium C14-16 olefin sulfonate, cocamidopropyl betaine, glycerin, sodium chloride, acrylates copolymer, polysorbate 20, fragrance, C12-15 alkyl lactate, sodium hydroxide, disodium EDTA, benzalkonium chloride, polyvinyl alcohol, cocamidopropyl PG-dimonium chloride phosphate, benzophenone-4, neopentyl glycol dicaprylate/dicaprate, carrageenan, agar, Citrus grandis (Grapefruit) fruit extract, ascorbyl palmitate, butylene glycol, mica, titanium dioxide, iron oxides, red 30, red 40, ext. violet 2

ADVERSE REACTION

Satisfaction guaranteed - For questions or comments please call 1-888-287-1915.

Empty before recycling

Plastic Bottle

how2recycle.info

Distributed by: Walmart Inc., Bentonville, AR 72716

*This product is not manufactured or distributed by Kenvue, Inc., owner of the registered trademark Neutrogena ®Body Clear ®Body Wash Pink Graperfuit.

principal display panel

NDC 49035-073-23

equate ™

beauty

Compare to Neutrogena ®Body Clear ®Body Wash Pink Grapefruit*

Clarifying Pink Grapefruit Body Wash

Salicylic acid acne medication

Cleanse

Helps Fight Body Breakouts

With naturally derived grapefruit extract

PARABEN FREE

8.5 FL OZ (251 mL)